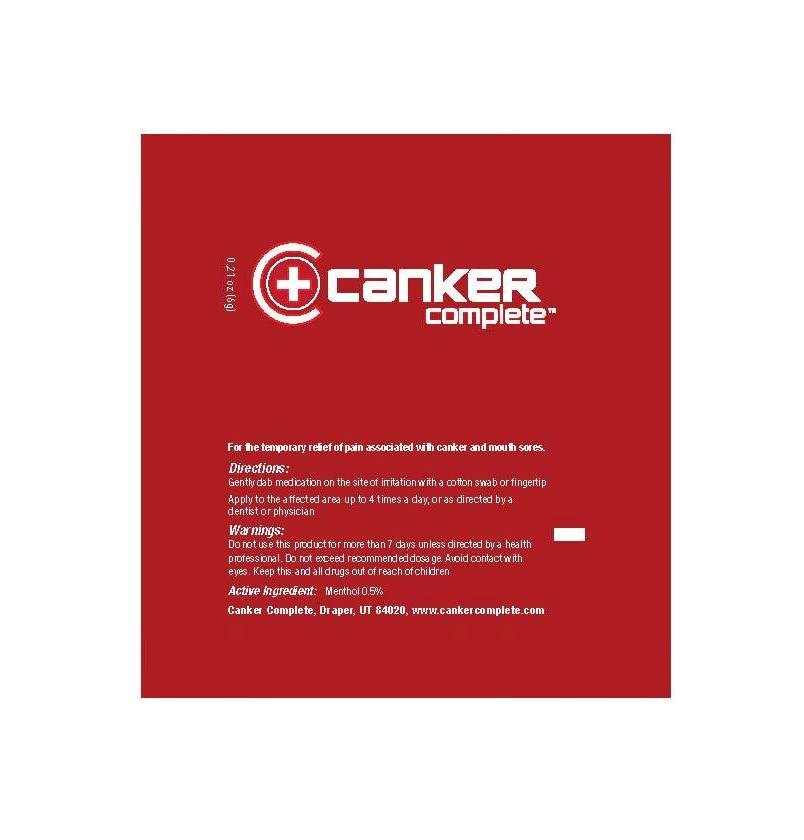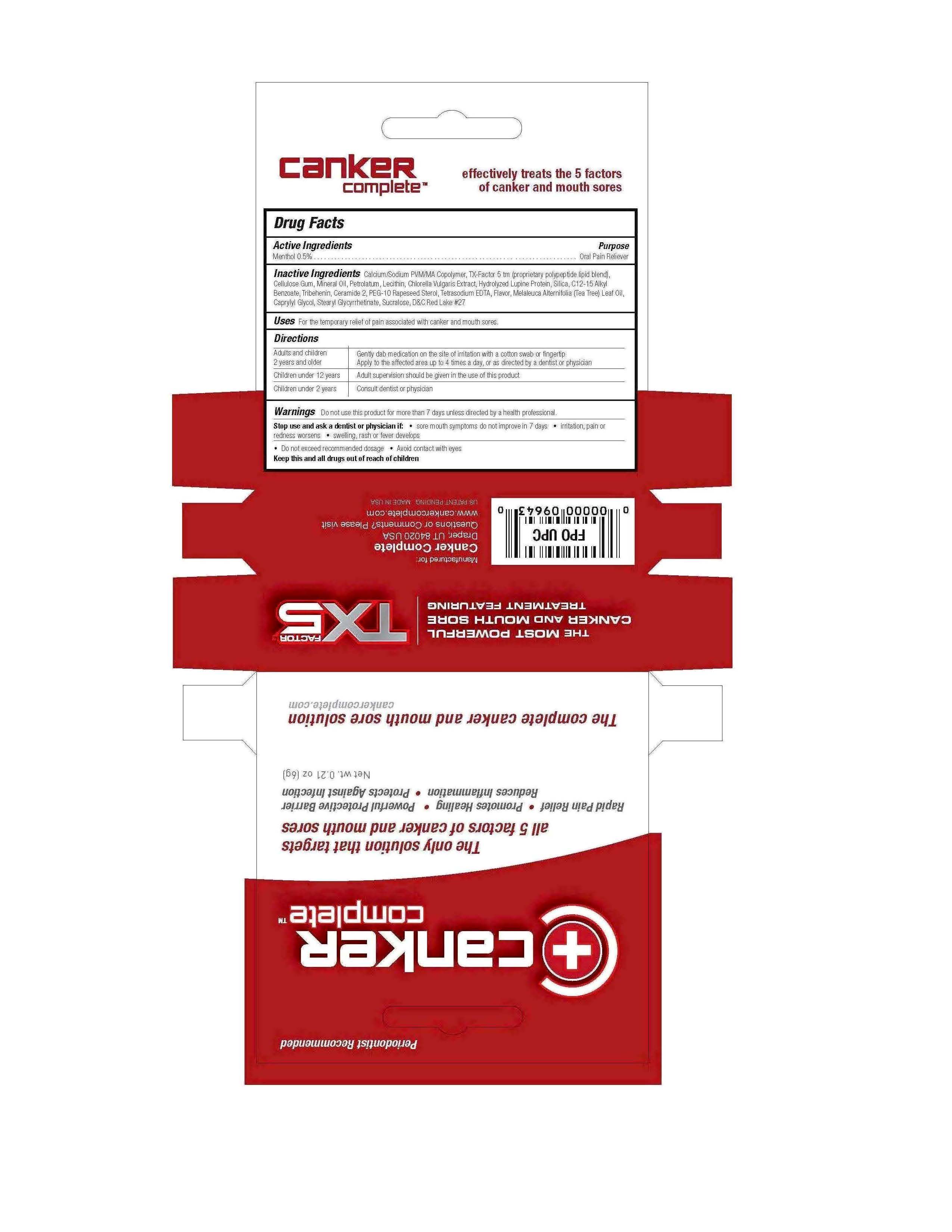 DRUG LABEL: Canker Complete
NDC: 44717-890 | Form: CREAM
Manufacturer: Wasatch Product Development
Category: otc | Type: HUMAN OTC DRUG LABEL
Date: 20170522

ACTIVE INGREDIENTS: Menthol 0.5 g/100 g
INACTIVE INGREDIENTS: CARBOXYMETHYLCELLULOSE SODIUM; MINERAL OIL; PETROLATUM; CHLORELLA VULGARIS; SILICON DIOXIDE; ALKYL (C12-15) BENZOATE; TRIBEHENIN; CERAMIDE 2; PEG-10 RAPESEED STEROL; EDETATE SODIUM; TEA TREE OIL; CAPRYLYL GLYCOL; SUCRALOSE

Canker Complete

Active ingredient Purpose

Menthol 0.5% Oral Pain Reliever

PURPOSE

Uses For the temporary relief of pain associated with canker and mouth sores

KEEP OUT OF REACH OF CHILDREN

Keep this and all drugs out of reach of children

Stop use and ask a dentist or physician if

- Sore mouth symptoms do not improve in 7 days

- Irritation, pain or redness worsens

- Swelling, rash or fever develops

Do not use this product for more than 7 days unless directed by a health professional

Directions

Adults and children 2 years and older Gently dab medication on the site of irritation with a cotton swab or fingertip

Apply to the affected area up to 4 times a day, or as directed by a dentist or physician

Children under 12 years Adult supervision should be given in the use of this product

Children under 2 years Consult dentist or physician

Inactive ingredients:

Calcium/Sodium PVM/MA Copolymer, TX-Factor 5 tm (propietary polypeptide lipid blend), Cellulose Gum, Mineral Oil, Petrolatum, Lecithin, Chlorella Vulgaris Extract, Hydrolyzed Lupine Protein, Silica, C12-15 Alkyl Benzoate, Tribehenin, Ceramide 2, PEG-10 Rapeseed Sterol, Tetrasodium EDTA, Flavor, Melaleuca Alternafolia (Tea Tree) Leaf Oil, Caprylyl Glycol, Stearyl Glycyrrhetinate, Sucralose, DC Red Lake 27

PACKAGE LABEL

Canker Complete Net wt. .21oz (6g)